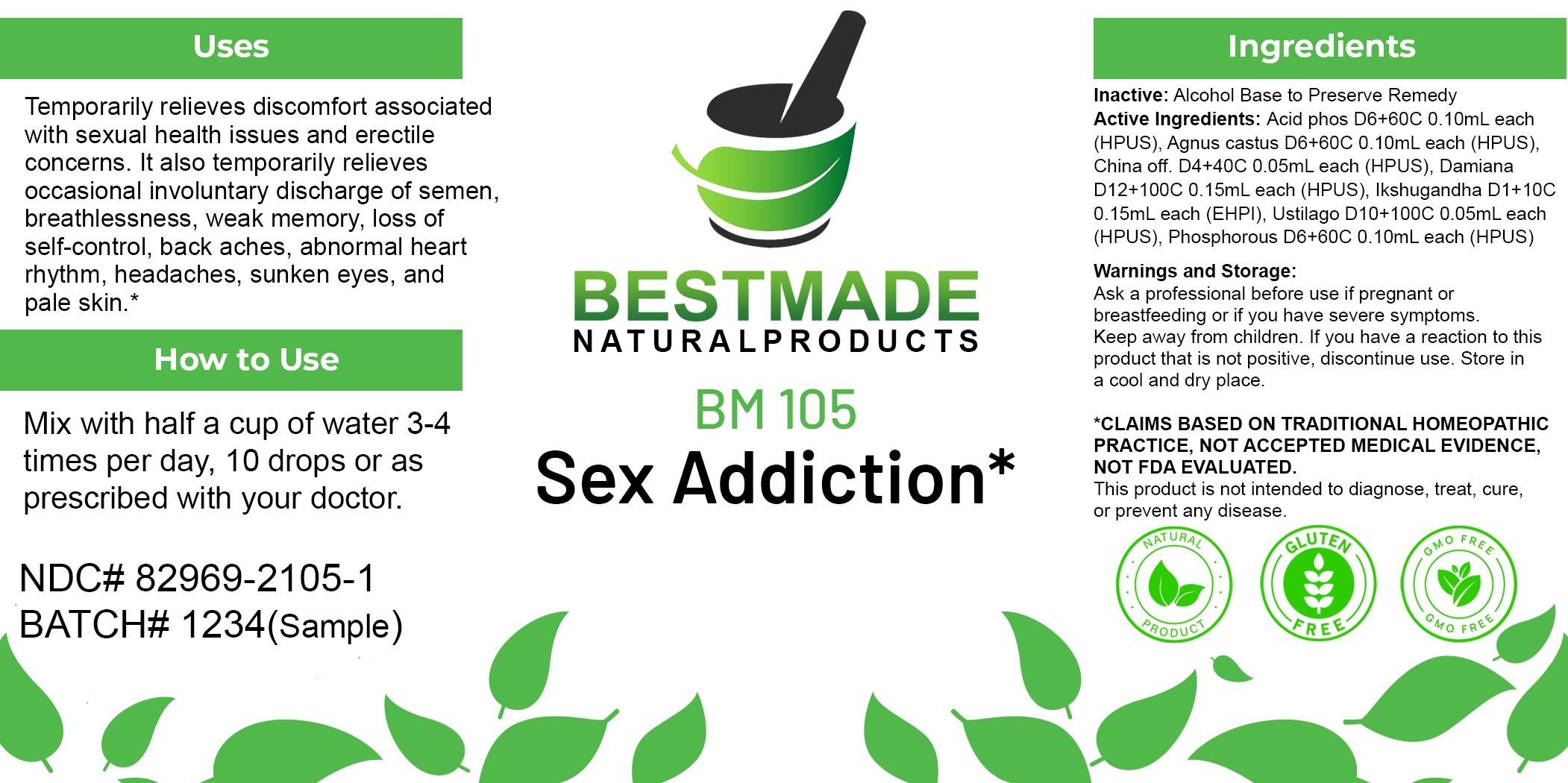 DRUG LABEL: Bestmade Natural Products BM105
NDC: 82969-2105 | Form: LIQUID
Manufacturer: Bestmade Natural Products
Category: homeopathic | Type: HUMAN OTC DRUG LABEL
Date: 20250207

ACTIVE INGREDIENTS: PHOSPHORIC ACID 30 [hp_C]/30 [hp_C]; CINCHONA OFFICINALIS BARK 30 [hp_C]/30 [hp_C]; PHOSPHORUS 30 [hp_C]/30 [hp_C]; TRIBULUS TERRESTRIS WHOLE 30 [hp_C]/30 [hp_C]; TURNERA DIFFUSA LEAFY TWIG 30 [hp_C]/30 [hp_C]; USTILAGO MAYDIS 30 [hp_C]/30 [hp_C]; CHASTE TREE FRUIT 30 [hp_C]/30 [hp_C]
INACTIVE INGREDIENTS: ALCOHOL 30 [hp_C]/30 [hp_C]

BM105

DOSAGE AND ADMINISTRATION

How to Use

Mix with half a cup of water 3-4 times per day. Ages 12 or older, 10 drops. Ages 12-2, 5 drops. Ages 2 and under, consult your Doctor.

Inactive:

Alcohol Base to Preserve Product

Active Ingredients:

Acid phos D6+60C 0.10mL each (HPUS), Agnus castus D6+60C 0.10mL each (HPUS), China off. D4+40C 0.05mL each (HPUS), Damiana D12+100C 0.15mL each (HPUS), Ikshugandha D1+10C 0.15mL each (EHPI), Ustilago D10+100C 0.05mL each (HPUS), Phosphorous D6+60C 0.10mL each (HPUS)

Uses
Temporarily relieves discomfort associated with sexual health issues and erectile concerns. It also temporarily relieves occasional involuntary discharge of semen, breathlessness, weak memory, loss of self-control, back aches, abnormal heart rhythm, headaches, sunken eyes, and pale skin.*

Uses
Temporarily relieves discomfort associated with sexual health issues and erectile concerns. It also temporarily relieves occasional involuntary discharge of semen, breathlessness, weak memory, loss of self-control, back aches, abnormal heart rhythm, headaches, sunken eyes, and pale skin.*

KEEP OUT OF REACH OF CHILDREN

Warnings and Storage:

Ask a professional before use if pregnant or breastfeeding or if you have severe symptoms.

Keep away from children. If you have a reaction to this product that is not positive, discontinue use. Store in a cool and dry place

*CLAIMS BASED ON TRADITIONAL HOMEOPATHIC PRACTICE, NOT ACCEPTED MEDICAL EVIDENCE NOT FDA EVALUATED.
This product is not intended to diagnose, treat, cure, or prevent any disease.

Warnings and Storage:

Ask a professional before use if pregnant or breastfeeding or if you have severe symptoms.

Keep away from children. If you have a reaction to this product that is not positive, discontinue use. Store in a cool and dry place

*CLAIMS BASED ON TRADITIONAL HOMEOPATHIC PRACTICE, NOT ACCEPTED MEDICAL EVIDENCE NOT FDA EVALUATED.
This product is not intended to diagnose, treat, cure, or prevent any disease.

Entire package label